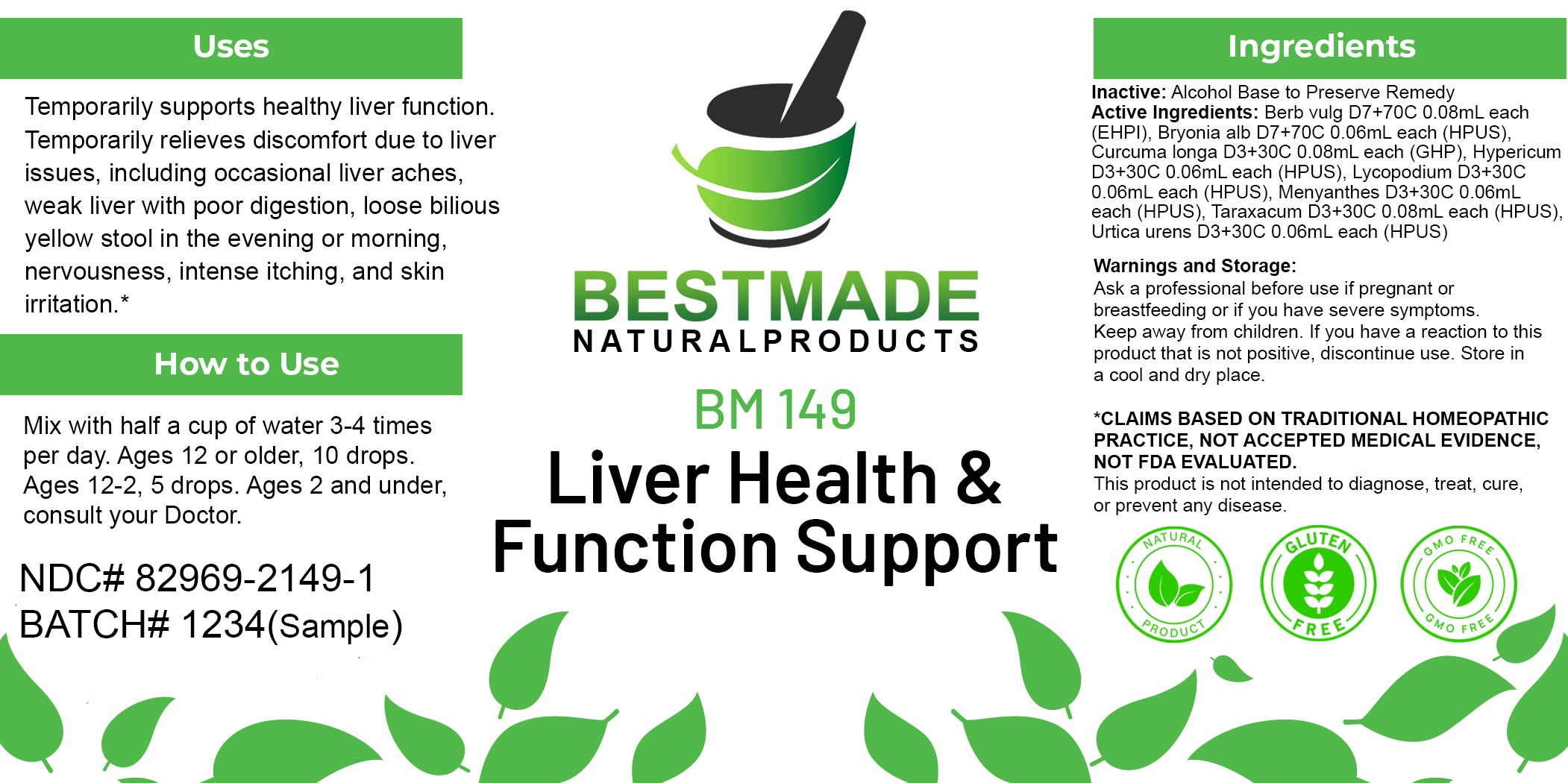 DRUG LABEL: Bestmade Natural Products BM149
NDC: 82969-2149 | Form: LIQUID
Manufacturer: Bestmade Natural Products
Category: homeopathic | Type: HUMAN OTC DRUG LABEL
Date: 20250218

ACTIVE INGREDIENTS: URTICA URENS WHOLE 30 [hp_C]/30 [hp_C]; MENYANTHES TRIFOLIATA WHOLE 30 [hp_C]/30 [hp_C]; TURMERIC 30 [hp_C]/30 [hp_C]; LYCOPODIUM CLAVATUM SPORE 30 [hp_C]/30 [hp_C]; BERBERIS VULGARIS ROOT BARK 30 [hp_C]/30 [hp_C]; TARAXACUM OFFICINALE 30 [hp_C]/30 [hp_C]; BRYONIA ALBA ROOT 30 [hp_C]/30 [hp_C]; HYPERICUM PERFORATUM WHOLE 30 [hp_C]/30 [hp_C]
INACTIVE INGREDIENTS: ALCOHOL 30 [hp_C]/30 [hp_C]

BM149

DOSAGE AND ADMINISTRATION

How to Use

Mix with half a cup of water 3-4 times per day. Ages 12 or older, 10 drops. Ages 12-2, 5 drops. Ages 2 and under, consult your Doctor.

Inactive:

Alcohol Base to Preserve Product

ACTIVE INGREDIENTS

Berb vulg D7+70C 0.08mL each (EHPI), Bryonia alb D7+70C 0.06mL each (HPUS), Curcuma longa D3+30C 0.08mL each (GHP), Hypericum D3+30C 0.06mL each (HPUS), Lycopodium D3+30C 0.06mL each (HPUS), Menyanthes D3+30C 0.06mL each (HPUS), Taraxacum D3+30C 0.08mL each (HPUS), Urtica urens D3+30C 0.06mL each (HPUS)

Uses
Temporarily supports healthy liver function. Temporarily relieves discomfort due to liver issues, including occasional liver aches,
weak liver with poor digestion, loose, bilious, yellow stool in the evening or morning, nervousness, intense itching, and skin irritation.*

KEEP OUT OF REACH OF CHILDREN

Warnings and Storage:

Ask a professional before use if pregnant or breastfeeding or if you have severe symptoms.

Keep away from children. If you have a reaction to this product that is not positive, discontinue use. Store in a cool and dry place

*CLAIMS BASED ON TRADITIONAL HOMEOPATHIC PRACTICE, NOT ACCEPTED MEDICAL EVIDENCE NOT FDA EVALUATED.
This product is not intended to diagnose, treat, cure, or prevent any disease.

Uses
Temporarily supports healthy liver function. Temporarily relieves discomfort due to liver issues, including occasional liver aches,
weak liver with poor digestion, loose, bilious, yellow stool in the evening or morning, nervousness, intense itching, and skin irritation.*

Warnings and Storage:

Ask a professional before use if pregnant or breastfeeding or if you have severe symptoms.

Keep away from children. If you have a reaction to this product that is not positive, discontinue use. Store in a cool and dry place

*CLAIMS BASED ON TRADITIONAL HOMEOPATHIC PRACTICE, NOT ACCEPTED MEDICAL EVIDENCE NOT FDA EVALUATED.
This product is not intended to diagnose, treat, cure, or prevent any disease.

Entire package label